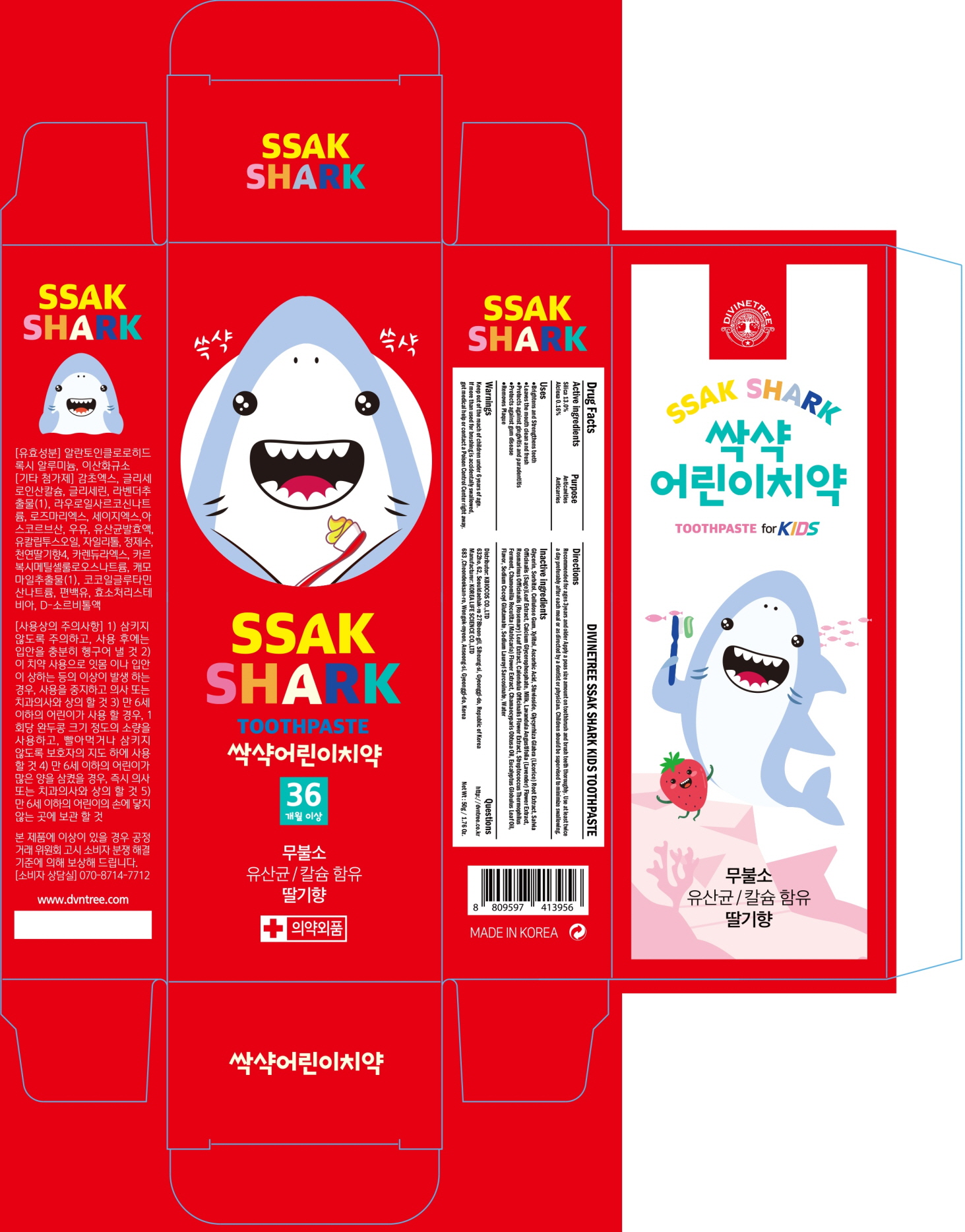 DRUG LABEL: DIVINETREE SSAK SHARK KIDS TOOTH
NDC: 73494-010 | Form: PASTE, DENTIFRICE
Manufacturer: K.biocos
Category: otc | Type: HUMAN OTC DRUG LABEL
Date: 20191204

ACTIVE INGREDIENTS: SILICON DIOXIDE 6.50 g/50 g; ALCLOXA 0.08 g/50 g
INACTIVE INGREDIENTS: Glycerin; SORBITOL

ACTIVE INGREDIENT

Active Ingredient: Silica 13.0%, Alcloxa 0.16%

INACTIVE INGREDIENT

Inactive Ingredients:

Glycerin, Sorbitol, Cellulose Gum, Xylitol, Ascorbic Acid, Stevioside, Glycyrrhiza Glabra (Licorice) Root Extract, Salvia Officinalis (Sage) Leaf Extract, Calcium Glycerophosphate, Milk, Lavandula Angustifolia (Lavender) Flower Extract, Rosmarinus Officinalis (Rosemary) Leaf Extract, Calendula Officinalis Flower Extract, Streptococcus Thermophilus Ferment, Chamomilla Recutita (Matricaria) Flower Extract, Chamaecyparis Obtusa Oil, Eucalyptus Globulus Leaf Oil, Flavor, Sodium Cocoyl Glutamate, Sodium Lauroyl Sarcosinate, Water

PURPOSE

Purpose: Anticavities, Anticarries

WARNINGS

Keep out of the reach of children under 6 years of age.
If more than used for brushing is accidentally swallowed, get medical help or contact a Poison Control Center right away.

KEEP OUT OF REACH OF CHILDREN

Keep out of the reach of children under 6 years of age.

Uses

Brightens and Strengthens teeth
Leaves the mouth clean and fresh
Protects against gingivitis and paradentitis
Protects against gum disease
Removes Plaque

Directions

Recommended for ages 3years and older
Apply a peas size amount on toothbrush and brush teeth thoroughly. Use at least twice a day preferably after each meal or as directed by a dentist or physician.
Children should be supervised to minimize swallowing.